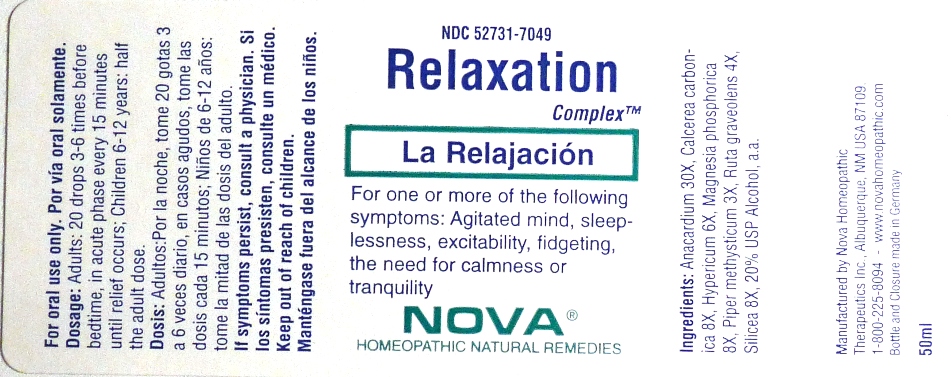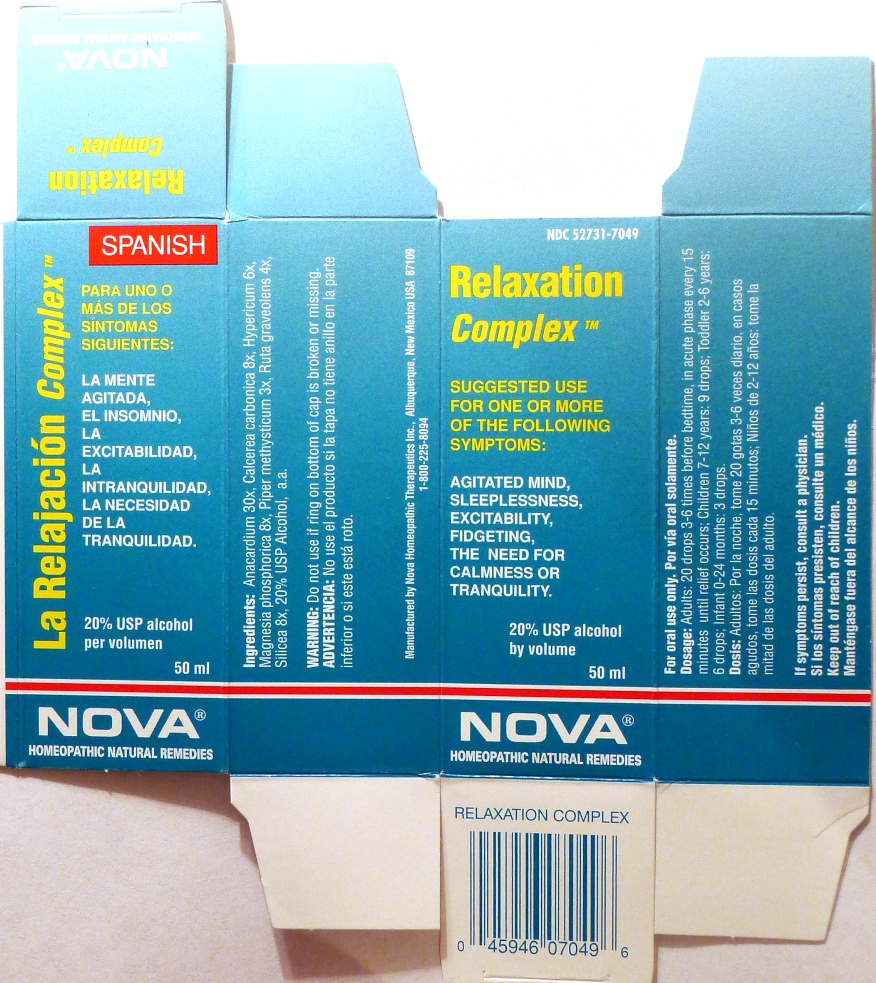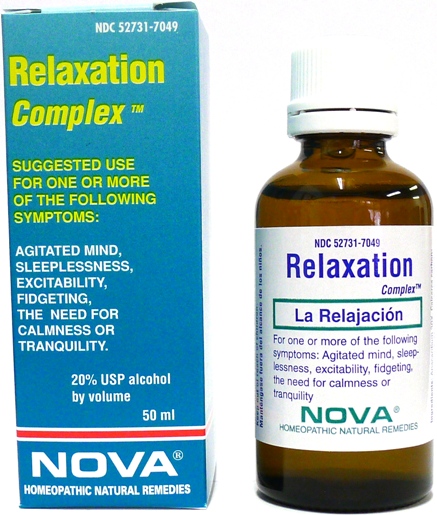 DRUG LABEL: Relaxation Complex
NDC: 52731-7049 | Form: LIQUID
Manufacturer: Nova Homeopathic Therapeutics, Inc.
Category: homeopathic | Type: HUMAN OTC DRUG LABEL
Date: 20110601

ACTIVE INGREDIENTS: SEMECARPUS ANACARDIUM JUICE 30 [hp_X]/1 mL; OYSTER SHELL CALCIUM CARBONATE, CRUDE 8 [hp_X]/1 mL; ST. JOHN'S WORT 6 [hp_X]/1 mL; MAGNESIUM PHOSPHATE, DIBASIC TRIHYDRATE 8 [hp_X]/1 mL; PIPER METHYSTICUM ROOT 3 [hp_X]/1 mL; RUTA GRAVEOLENS FLOWERING TOP 4 [hp_X]/1 mL; SILICON DIOXIDE 8 [hp_X]/1 mL
INACTIVE INGREDIENTS: ALCOHOL

Relaxation Complex

Purpose:

Suggested use for one or more of the following symptoms:
Agitated mind, sleeplessness, excitability, fidgeting, the need for calmness or tranquility.

Usage and Dosage:

For oral use only.

DOSAGE AND ADMINISTRATION

Adults:
In Acute Phase:
20 drops, every 15 minutes until relief occurs
When Relief Occurs:
20 drops, 3-6 times before bedtime
Children 6-12 years:
Half the adult dose.

Warnings:

Keep out of reach of children.

WARNINGS

If symptoms persist, consult a physician.
Do not use if ring on bottom of cap is broken or missing.

Active Ingredients:

Anacardium 30x, Calcerea carbonica 8x, Hypericum 6x, Magnesia phosphorica 8x, Piper methysticum 3x, Ruta graveolens 4x, Silicea 8x

Inactive Ingredients:

Alcohol, 20% USP

QUESTIONS

Manufactured by Nova Homeopathic Therapeutics Inc., Albuquerque, New Mexico USA 87109
1-800-225-8094

PACKAGE LABEL

Relaxation Complex Product

Relaxation Complex Bottle Label

Relaxation Complex Box